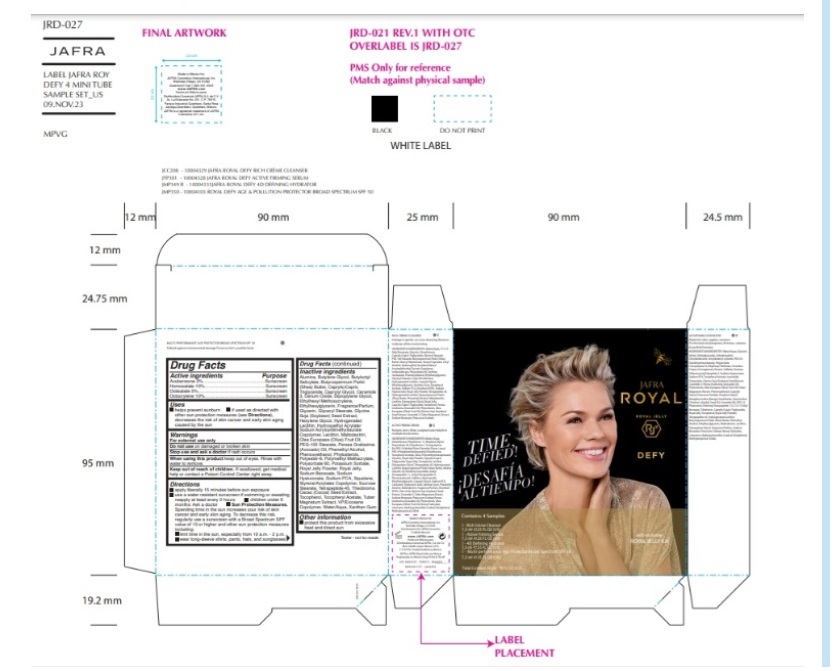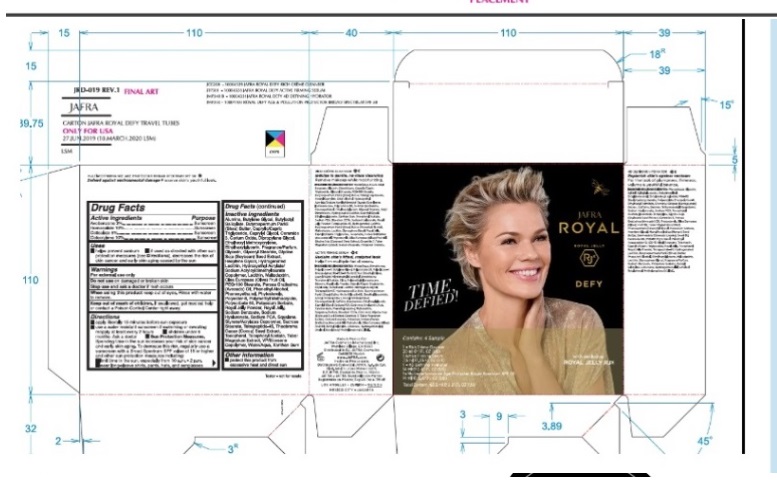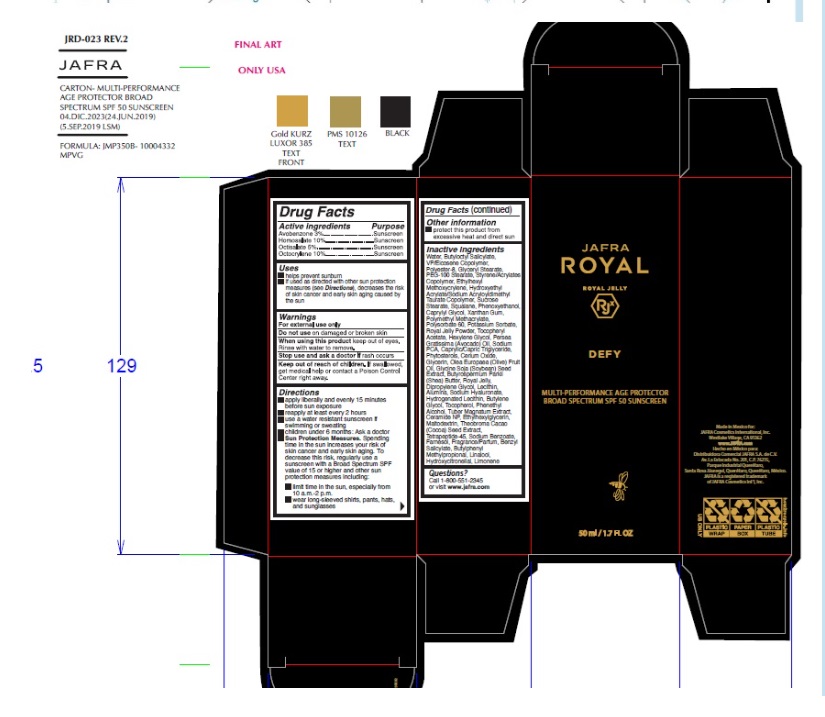 DRUG LABEL: Jafra Royal Defy Sample Kit
NDC: 68828-760 | Form: KIT | Route: TOPICAL
Manufacturer: Distribuidora Comercial Jafra, S.A. de C.V.
Category: otc | Type: HUMAN OTC DRUG LABEL
Date: 20250122

ACTIVE INGREDIENTS: AVOBENZONE 3 g/100 mL; HOMOSALATE 10 g/100 mL; OCTISALATE 5 g/100 mL; OCTOCRYLENE 10 g/100 mL
INACTIVE INGREDIENTS: STYRENE/ACRYLAMIDE COPOLYMER (500000 MW); SUCROSE STEARATE; CERIC OXIDE; ALUMINUM OXIDE; VINYLPYRROLIDONE/EICOSENE COPOLYMER; GLYCERIN; ETHYLHEXYLGLYCERIN; ETHYLHEXYL METHOXYCRYLENE; BUTYLOCTYL SALICYLATE; PHENYLETHYL ALCOHOL; POLYESTER-8 (1400 MW, CYANODIPHENYLPROPENOYL CAPPED); CERAMIDE NP; BUTYLENE GLYCOL; POLYSORBATE 60; PHENOXYETHANOL; DIPROPYLENE GLYCOL; POTASSIUM SORBATE; HYDROGENATED SOYBEAN LECITHIN; AVOCADO OIL; POLY(METHYL METHACRYLATE; 450000 MW); WATER; COCOA; GLYCERYL MONOSTEARATE; PEG-100 STEARATE; HEXYLENE GLYCOL; HYDROXYETHYL ACRYLATE/SODIUM ACRYLOYLDIMETHYL TAURATE COPOLYMER (100000 MPA.S AT 1.5%); LECITHIN, SOYBEAN; MALTODEXTRIN; SQUALANE; TOCOPHEROL; XANTHAN GUM; MEDIUM-CHAIN TRIGLYCERIDES; CAPRYLYL GLYCOL; HYALURONATE SODIUM; SOYBEAN; SODIUM BENZOATE; ROYAL JELLY; SODIUM PYRROLIDONE CARBOXYLATE; .ALPHA.-TOCOPHEROL ACETATE; SHEA BUTTER; OLIVE OIL; BENZYL SALICYLATE; BUTYLPHENYL METHYLPROPIONAL; LINALOOL, (+/-)-; HYDROXYCITRONELLAL; LIMONENE, (+)-; FARNESOL

Active Ingredients

Avobenzone 3%

Homosalate 10%

Octisalate 5%

Octocrylene 10%

Purpose

Sunscreen

Uses

Helps prevent sunburn
If used as directed with other sun protection measures (see Directions), decreases the risk of skin cancer and early skin aging caused by the sun.

Warnings

For external use only

Do not useon damaged or broken skin

When using this productkeep out of eyes. Rinse with water to remove.

Stop use and ask a doctorif rash occurs

Keep out of reach of children.If swallowed, get medical help or contact a Poison Control Center right away.

Directions

- apply liberally and evenly 15 minutes before sun exposure
- reapply at least every 2 hours.
- use a water-resistant sunscreen if swimming or sweating
- children under 6 months : Ask a doctor
- Sun Protection Measures.Spending time in the sun increases your risk of skin cancer and early skin aging. To decrease this risk, regularly use a sunscreen with a Broad Spectrum SPF value of 15 or higher and other sun protection measures including:
- limit time in the sun, especially from 10 a.m. – 2 p.m.
- wear long-sleeved shirts, pants, hats, and sunglasses

Other information

Protect this product from excessive heat and direct sun

Inactive ingredients

Water, Butyloctyl Salicylate, VP/Eicosene Copolymer, Polyester-8, Glyceryl Stearate,PEG-100 Stearate, Styrene/Acrylates Copolymer, Ethylhexyl Methoxycrylene,Hydroxyethyl Acrylate/Sodium Acryloyldimethyl Taurate Copolymer, Sucrose Stearate,Squalane, Phenoxyethanol, Caprylyl Glycol, Xanthan Gum, Polymethyl Methacrylate,Polysorbate 60, Potassium Sorbate, Royal Jelly Powder, Tocopheryl Acetate, Hexylene Glycol, Persea Gratissima (Avocado) Oil, Sodium PCA, Caprylic/Capric Triglyceride,Phytosterols, Cerium Oxide, Glycerin, Olea Europaea (Olive) Fruit Oil, Glycine Soja(Soybean) Seed Extract, Butyrospermum Parkii (Shea) Butter, Royal Jelly, Dipropylene Glycol, Lecithin, Alumina, Sodium Hyaluronate, Hydrogenated Lecithin, Butylene Glycol, Tocopherol, Phenethyl Alcohol, Tuber Magnatum Extract, Ceramide NP, Ethylhexylglycerin, Maltodextrin, Theobroma Cacao (Cocoa) Seed Extract, Tetrapeptide-45, Sodium Benzoate, Farnesol, Fragrance/Parfum, Benzyl Salicylate, Butylphenyl Methylpropional, Linalool, Hydroxycitronellal, Limonene

Questions?

Call 1-800-551-2345
or visit www.jafra.com